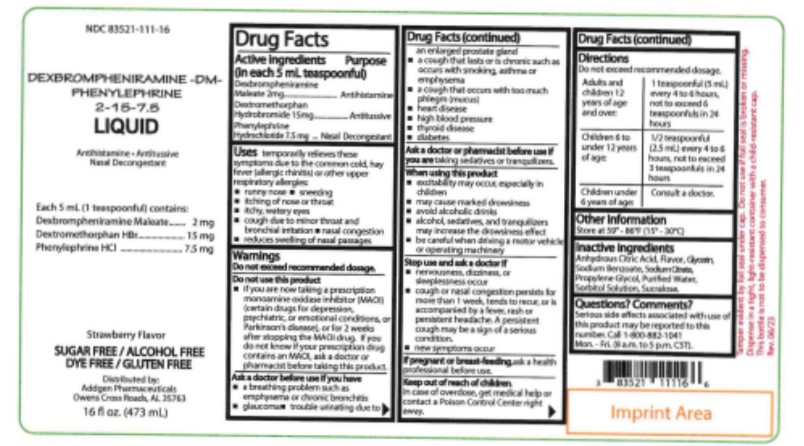 DRUG LABEL: Dexbrompheniramine-DM-Phenylephrine 2-15-7.5
NDC: 83521-111 | Form: LIQUID
Manufacturer: AddGen Pharmaceuticals, Inc.
Category: otc | Type: HUMAN OTC DRUG LABEL
Date: 20230709

ACTIVE INGREDIENTS: DEXBROMPHENIRAMINE MALEATE 2 mg/5 mL; DEXTROMETHORPHAN HYDROBROMIDE 15 mg/5 mL; PHENYLEPHRINE HYDROCHLORIDE 7.5 mg/5 mL
INACTIVE INGREDIENTS: CITRIC ACID MONOHYDRATE; GLYCERIN; PROPYLENE GLYCOL; WATER; SODIUM BENZOATE; SODIUM CITRATE; SACCHARIN SODIUM; SORBITOL

Active ingredients

(in each 5 mL teaspoonful)
Dexbrompheniramine Maleate 2 mg
Dextromethorphan Hydrobromide 15 mg
Phenylephrine Hydrochloride 7.5mg

Purpose

Antihistamine
Antitussive
Nasal Decongestant

Uses

temporarily relieves these symptoms due to the common cold, hay fever (allergic rhinitis) or other upper respiratory allergies:

- runny nose
- sneezing
- itching of nose or throat
- itchy, watery eyes
- cough due to minor throat and bronchial irritation
- nasal congestion
- reduces swelling of nasal passages

Warnings

Do not exceed recommended dosage.

Do not use

this product

- if you are now taking a prescription monoamine oxidase inhibitor (MAOI) (certain drugs for depression, psychiatric, or emotional conditions, or Parkinson's disease), or for 2 weeks after stopping the MAOI drug. If you do not know if your prescription drug contains an MAOI, ask a doctor or pharmacist before taking this product.

Ask a doctor before use

if you have

- a breathing problem such as emphysema or chronic bronchitis
- glaucoma
- trouble urinating due to an enlarged prostate gland
- a cough that lasts or is chronic such as occurs with smoking, asthma or emphysema
- a cough that occurs with too much phlegm (mucus)
- heart disease
- high blood pressure
- thyroid disease
- diabetes

Ask a doctor or pharmacist before use

if you are

taking sedatives or tranquilizers.

When using this product

- excitability may occur, especially in children
- may cause marked drowsiness
- avoid alcoholic drinks
- alcohol, sedatives, and tranquilizers may increase the drowsiness effect
- be careful when driving a motor vehicle or operating machinery

Stop use and ask a doctor if

- nervousness, dizziness, or sleeplessness occur
- cough or nasal congestion persists for more than 1 week, tends to recur, or is accompanied by a fever, rash, or persistent headache. A persistent cough may be a sign of a serious condition.
- new symptoms occur

If pregnant or breast-feeding,

ask a health professional before use.

Keep out of reach of children.

In case of overdose, get medical help or contact a Poison Control Center right away.

Directions

Do not exceed recommended dosage.

Adults and children 12 years of age and over: | 1 teaspoonful (5 mL) every 4 to 6 hours, not to exceed 6 teaspoonfuls in a 24 hours
Children 6 to under 12 years of age: | 1/2 teaspoonful (2.5 mL) every 4 to 6 hours, not to exceed 3 teaspoonfuls in 24 hours
Children under 6 years of age: | Consult a doctor.

Other information

Store at 59° - 86°F (15° - 30°C)

Inactive ingredients

Anhydrous Citric Acid, Glycerin, Flavor, Propylene Glycol, Purified Water, Sodium Benzoate, Sodium Citrate Dihydrate, Sodium Saccharin, Sorbitol Solution.

Questions? Comments?

Serious side effects associated with use of this product may be reported to this number.
Call 1-800-882-1041
Mon. - Fri. (8 a.m. to 5 p.m. CST).